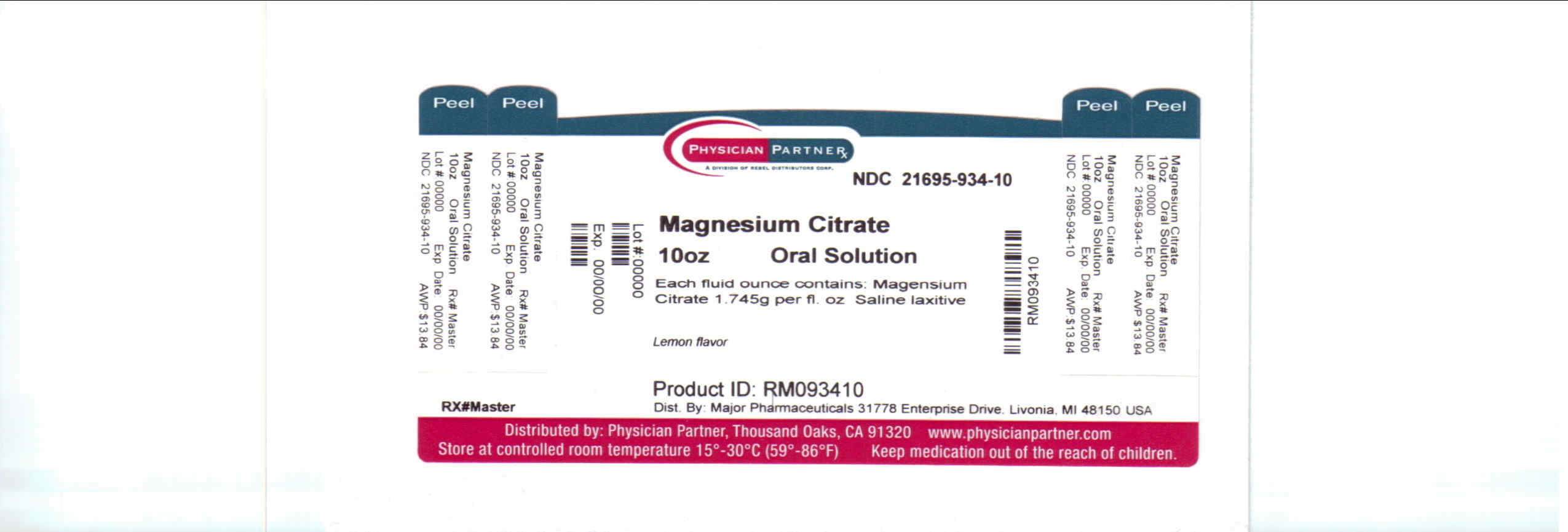 DRUG LABEL: Magnesium Citrate
NDC: 21695-934 | Form: LIQUID
Manufacturer: Rebel Distributors Corp
Category: otc | Type: HUMAN OTC DRUG LABEL
Date: 20110428

ACTIVE INGREDIENTS: MAGNESIUM CITRATE 2.62 g/100 mL
INACTIVE INGREDIENTS: water; CITRIC ACID MONOHYDRATE; SACCHARIN SODIUM ANHYDROUS; POTASSIUM BICARBONATE

Drug Facts

Active ingredient

Magnesium Citrate 1.745g per fl oz

Purpose

saline laxative

Uses

relieves occasional constipation (irregularity)

generally produces bowel movement in 1/2 to 6 hours

Warnings

ask a doctor before use if you have:

kidney disease

a magnesium restricted diet

stomach pain, nausea or vomiting

noticed a sudden change in bowel habits that lasts more than one week

Ask a doctor or pharmacist before use if you are

presently taking a prescription drug

when using this product

do not exceed the maximum recommended daily dosage in a 24 hour period

Stop use and ask a doctor if

you have rectal bleeding or no bowel movement after use .

These could be a sign of a serious condition.

you need to use a laxative more than one week.

If pregnant or breast feeding

ask a health professional before use.

keep this and all drugs out of the reach of children.

In case of accidental overdose, seek professional assistance or contact a poison control center immediately.

Directions

Adults and Children 12 years of age and older 1/2 to 1 bottle (10 fl oz). Drink a full 8 oz glass of liquid with each dose. The dose may be taken as a single daily dose or in divided doses.

children 6 to under 12 years of age 1/3 to 1/2 bottle with a full 8 oz glass of liquid.

children under 6 years of age consult a doctor

Other Information

store at controlled room temperature

protect from excessive heat and freezing

discard unused product within 24 hours of opening bottle

Inactive Ingredients

Citric acid, flavors, potassium bicarbonate, saccharin sodium, purified water

Questions or Comments?

1-866-534-4631